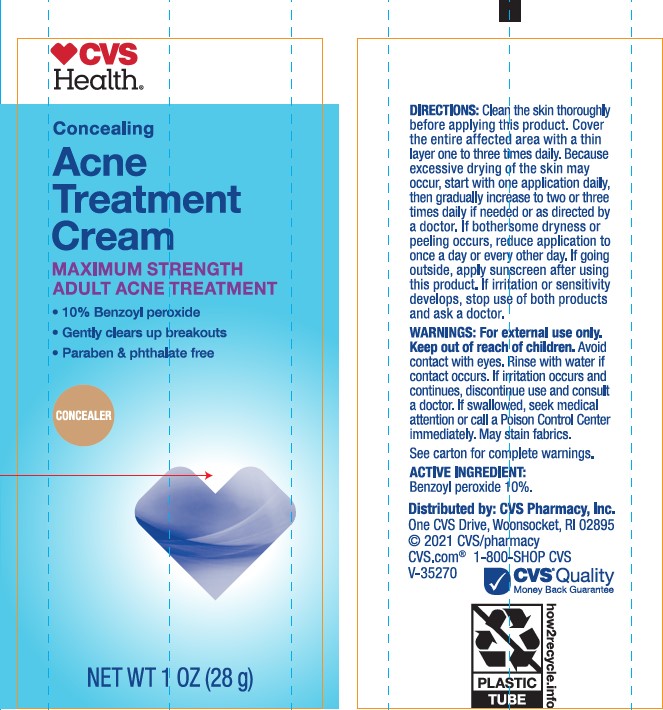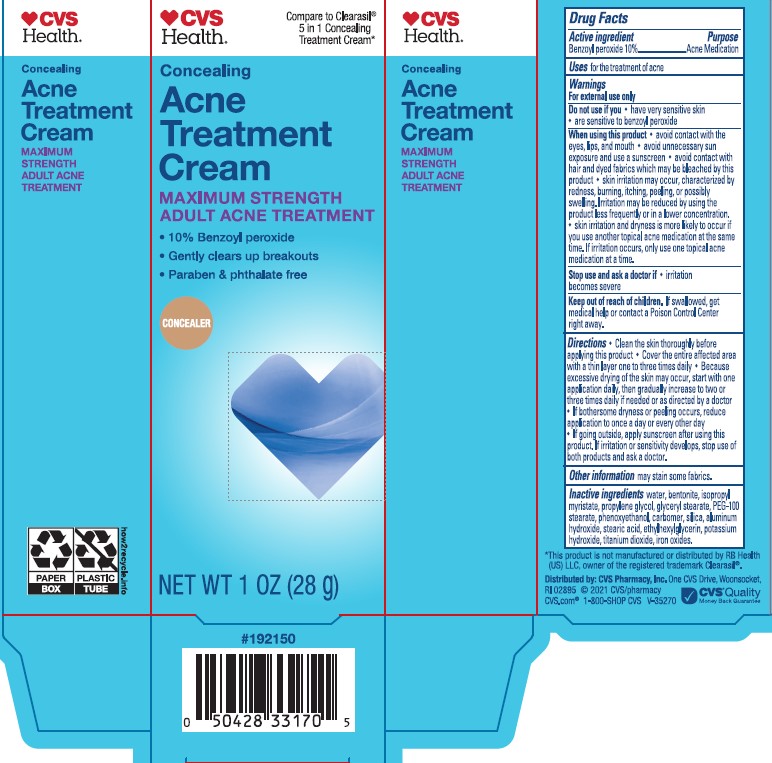 DRUG LABEL: CVS Health Concealing Acne Treatment Maximum Strength Adult Acne Treatment
NDC: 51316-047 | Form: CREAM
Manufacturer: CVS PHARMACY
Category: otc | Type: HUMAN OTC DRUG LABEL
Date: 20241017

ACTIVE INGREDIENTS: BENZOYL PEROXIDE 100 mg/1 g
INACTIVE INGREDIENTS: FERROSOFERRIC OXIDE; FERRIC OXIDE RED; ISOPROPYL MYRISTATE; CARBOMER HOMOPOLYMER TYPE B (ALLYL SUCROSE CROSSLINKED); WATER; GLYCERYL 1-STEARATE; ETHYLHEXYLGLYCERIN; STEARIC ACID; ALUMINUM HYDROXIDE; PROPYLENE GLYCOL; SILICON DIOXIDE; FERRIC OXIDE YELLOW; PHENOXYETHANOL; BENTONITE; POTASSIUM HYDROXIDE; PEG-100 STEARATE; TITANIUM DIOXIDE; CARBOMER INTERPOLYMER TYPE A (ALLYL SUCROSE CROSSLINKED)

CVS Health Concealing Acne Treatment Cream Maximum Strength Adult Acne Treatment

Active Ingredient

Benzoyl peroxide 10%

Purpose

Acne Medication

Uses

for the treatment of acne

Warnings

For external use only

Do not use if you

- have very sensitive skin
- are sensitive to benzoyl peroxide

When using this product:

- avoid unnecessary sun exposure and use a sunscreen
- avoid contact with the eyes, lips, and mouth
- avoid contact with hair and dyed fabrics which may be bleached by this product
- skin irritation may occur, characterized by redness, burning, itching, peeling, or possibly swelling. Irritation may be reduced by using the product less frequently or in a lower concentration.
- skin irritation and dryness is more likely to occur if you use another topical acne medication at the same time. If irritation occurs, only use one topical acne medication at a time.

Stop use and ask doctor if

- irritation becomes severe.

Keep out of the reach of children.

If swallowed, get medical help or contact a Poison Control Center right away.

Directions

- Clean the skin thoroughly before applying this product
- Cover the entire affected area with a thin layer one to three times daily
- Because excessive drying of the skin may occur, start with one application daily, then gradually increase to two to three times daily if needed or as directed by a doctor
- If bothersome dryness or peeling occurs, reduce application to once a day or every other day
- If going outside, apply sunscreen after using this product. If irritation or sensitivity develops, stop use of both products and ask a doctor.

Inactive Ingredients

Water, Bentonite, Isopropyl Myristate, Propylene Glycol, Glyceryl Stearate, PEG-100 Stearate, Phenoxyethanol, Carbomer, Silica, Aluminum Hydroxide, Stearic Acid, Ethylhexylglycerin, Potassium Hydroxide, Titanium Dioxide, Iron Oxides